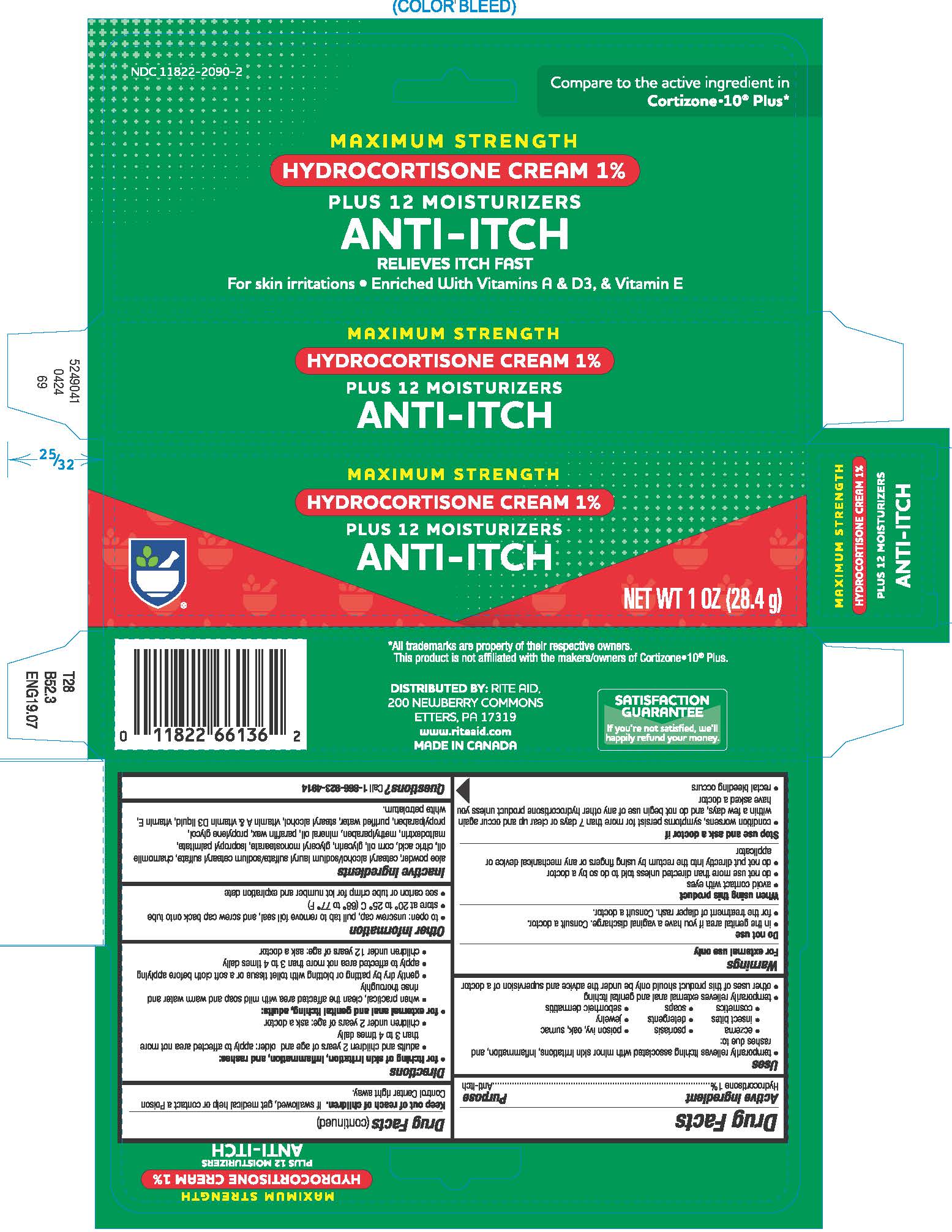 DRUG LABEL: Hydrocortisone

NDC: 11822-2090 | Form: CREAM
Manufacturer: RITE AID CORPORATION
Category: otc | Type: HUMAN OTC DRUG LABEL
Date: 20250728

ACTIVE INGREDIENTS: HYDROCORTISONE 1 g/100 g
INACTIVE INGREDIENTS: CETOSTEARYL ALCOHOL; SODIUM LAURYL SULFATE; SODIUM CETOSTEARYL SULFATE; CHAMOMILE FLOWER OIL; CITRIC ACID MONOHYDRATE; CORN OIL; GLYCERIN; GLYCERYL MONOSTEARATE; ISOPROPYL PALMITATE; MALTODEXTRIN; METHYLPARABEN; MINERAL OIL; PARAFFIN; PETROLATUM; PROPYLENE GLYCOL; PROPYLPARABEN; WATER; STEARYL ALCOHOL; VITAMIN A PALMITATE; CHOLECALCIFEROL; .ALPHA.-TOCOPHEROL ACETATE

Hydrocortisone Plus 12 Moisturizers

Drug Facts

Active ingredient

Hydrocortisone 1%

Purpose

Anti-itch

Uses

- temporarily relieves itching associated with minor skin irritations, inflammation, and rashes due to:
  - eczema
  - psoriasis
  - poison ivy, oak, sumac
  - insect bites
  - detergents
  - jewelry
  - cosmetics
  - soaps
  - seborrheic dermatitis
- temporarily relieves external anal and genital itching
- other uses of this product should only be under the advice and supervision of a doctor

Warnings

For external use only

Do not use

- in the genital area if you have a vaginal discharge. Consult a doctor.
- for the treatment of diaper rash. Consult a doctor.

When using this product

- avoid contact with eyes
- do not use more than directed unless told to do so by a doctor
- do not put directly into the rectum by using fingers or any mechanical device or applicator

Stop use and ask a doctor if

- condition worsens, symptoms persist for more than 7 days or clear up and occur again within a few days, and do not begin use of any other hydrocortisone product unless you have asked a doctor
- rectal bleeding occurs

Keep out of reach of children.If swallowed, get medical help or contact a Poison Control Center right away.

Directions

- for itching of skin irritation, inflammation, and rashes:
  - adults and children 2 years of age and older: apply to affected area not more than 3 to 4 times daily
  - children under 2 years of age: ask a doctor
- for external anal and genital itching, adults:
  - when practical, clean the affected area with mild soap and warm water and rinse thoroughly
  - gently dry by patting or blotting with toilet tissue or a soft cloth before applying
  - apply to affected area not more than 3 to 4 times daily
  - children under 12 years of age: ask a doctor

Other information

- to open: unscrew cap, pull tab to remove foil seal, and screw cap back onto tube
- store at 20° to 25° C (68° to 77° F)
- see carton or tube crimp for lot number and expiration date

Inactive ingredients

aloe powder, cetearyl alcohol/sodium lauryl sulfate/sodium cetearyl sulfate, chamomile oil, citric acid, corn oil, glycerin, glyceryl monostearate, isopropyl palmitate, maltodextrin, methylparaben, mineral oil, paraffin wax, propylene glycol, propylparaben, purified water, stearyl alcohol, vitamin A & vitamin D3 liquid, vitamin E, white petrolatum.

Questions?

Call 1-866-923-4914

DISTRIBUTED BY:
RITE AID, 200 NEWBERRY COMMONS ETTERS, PA 17319
www.riteaid.com

MADE IN CANADA

PRINCIPAL DISPLAY PANEL - 56.8 Tube Carton

MAXIMUM STRENGTH

HYDROCORTISONE CREAM 1%

PLUS 12 MOISTURIZERS

ANTI-ITCH

RELIEVES ITCH FAST

For skin irritations

• Enriched with vitamins A, D3 & Vitamin E

NET WT 1 OZ (28.4 g)